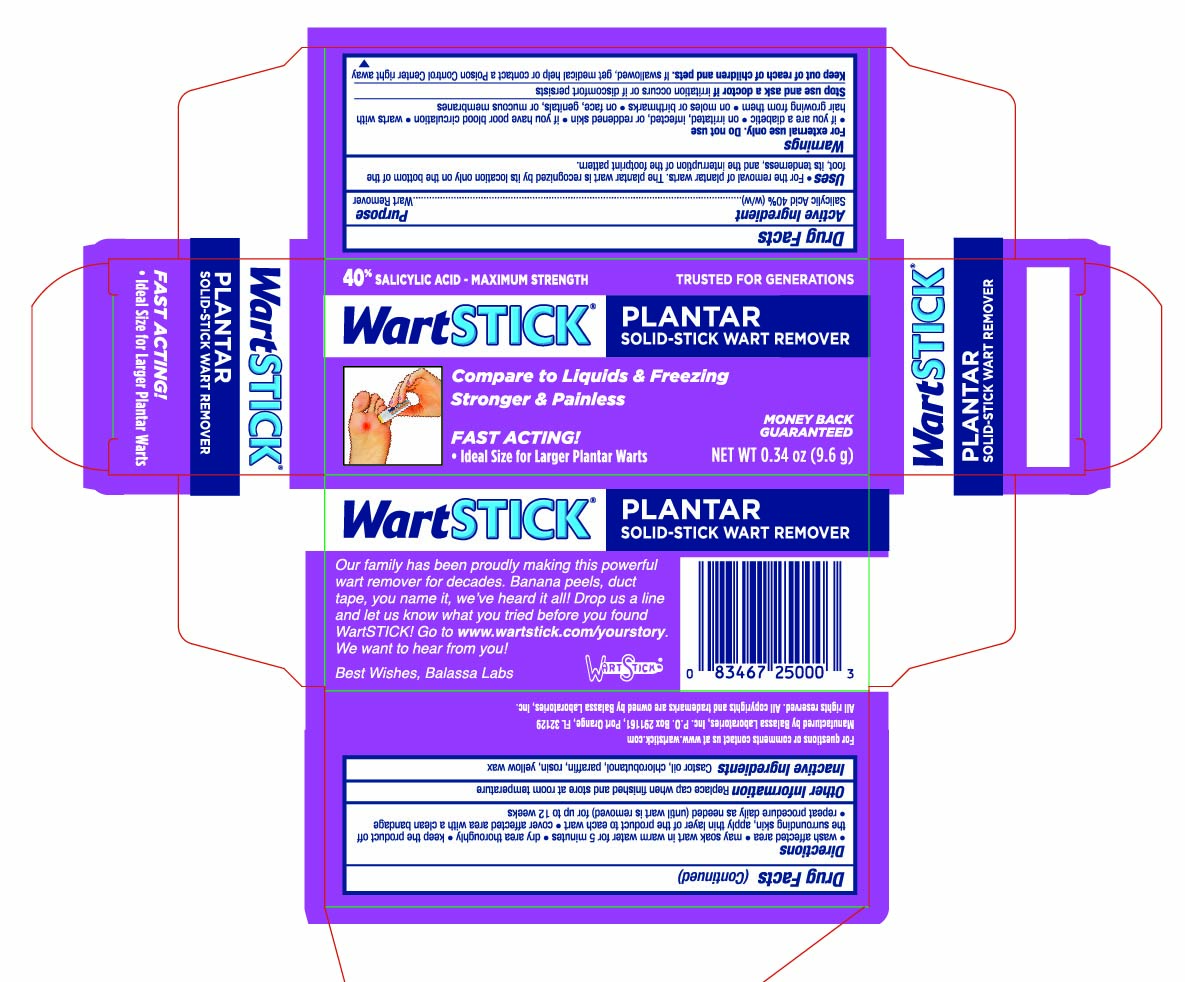 DRUG LABEL: WartStick Plantar
NDC: 10107-251 | Form: STICK
Manufacturer: Balassa Laboratories Inc.
Category: otc | Type: HUMAN OTC DRUG LABEL
Date: 20241001

ACTIVE INGREDIENTS: SALICYLIC ACID 0.4 g/1 g
INACTIVE INGREDIENTS: CASTOR OIL; CHLOROBUTANOL; YELLOW WAX; PARAFFIN; ROSIN

WartStick Plantar Wart Remover

Active Ingredient

Salicylic acid 40% (w/w)

Purpose

Wart remover

Uses

- For the removal of plantar warts. The plantar wart is recognized by its location only on the bottom of the foot, its tenderness, and the interruption of the footprint pattern.

Warnings

For external use only.

Do not use

- if you are a diabetic
- on irritated, infected, or reddened skin
- if you have poor blood circulation
- on warts with hair growing from them
- on moles or birthmarks
- on face, genitals, or mucous membranes

Stop use and ask a doctor if

irritation occurs or discomfort persists

Keep out of reach of children and pets.

If swallowed, get medical help or contact a Poison Control Center right away.

Directions

- Wash affected area
- May soak in warm water for 5 minutes
- Dry area thoroughly
- Keeping the product off the surrounding skin, apply a thin layer of the product to each wart
- Cover affected area with clean bandage
- Repeat procedure daily as needed (until wart is removed) for up to 12 weeks

Other Information

Replace cap when finished and store at room temperature

Inactive Ingredients

Castor oil, chlorobutanol, paraffin, rosin, yellow wax

PRINCIPAL DISPLAY PANEL - 9.6 g Tube in Carton - NDC 10107-251-02

40% SALICYLIC ACID MAXIMUM STRENGTH

TRUSTED FOR GENERATIONS

WartSTICK ® PLANTAR

SOLID-STICK WART REMOVER

Compare to Liquids and Freezing

Stronger & Painless

Fast Acting!

- Ideal Size for Larger Plantar Warts

MONEY BACK GUARANTEED

NET WT 0.34 OZ (9.6g)